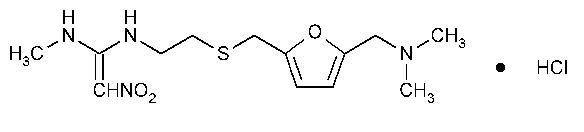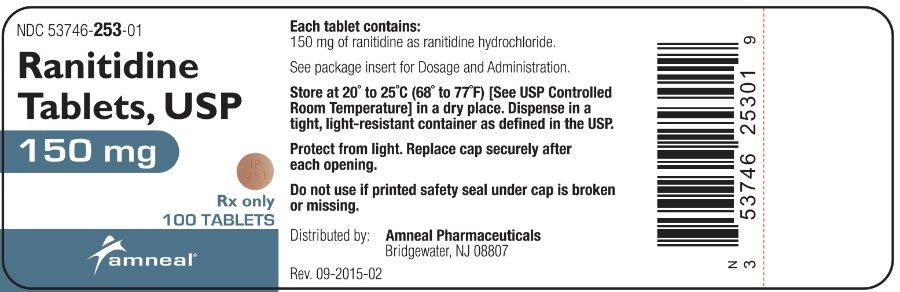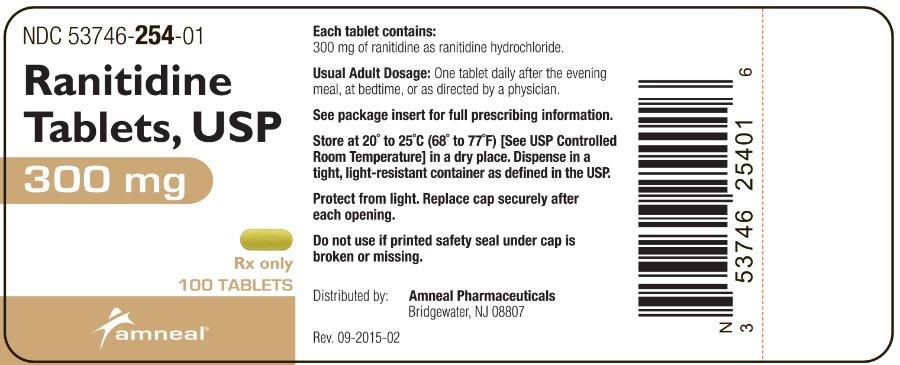 DRUG LABEL: Ranitidine
NDC: 53746-253 | Form: TABLET
Manufacturer: Amneal Pharmaceuticals of New York LLC
Category: prescription | Type: HUMAN PRESCRIPTION DRUG LABEL
Date: 20230111

ACTIVE INGREDIENTS: RANITIDINE HYDROCHLORIDE 150 mg/1 1

Ranitidine Tablets, USP
Rx Only

DESCRIPTION

The active ingredient in Ranitidine Tablets, USP 150 mg and Ranitidine Tablets, USP 300 mg is ranitidine hydrochloride (HCl), USP, a histamine H2-receptor antagonist. Chemically it is N[2-[[[5-[(dimethylamino)methyl]-2-furanyl]methyl]thio]ethyl]-N'-methyl-2-nitro-1,1-ethenediamine, HCl. It has the following structure:

The empirical formula is C13H22N4O3S·HCl, representing a molecular weight of 350.87. Ranitidine HCl is a white to pale yellow, granular substance that is soluble in water. It has a slightly bitter taste and sulfurlike odor.

Each Ranitidine Tablets, USP 150 mg for oral administration contains 167.4 mg of ranitidine HCl equivalent to 150 mg of ranitidine. Each tablet also contains the inactive ingredients colloidal silicon dioxide, croscarmellose sodium, hypromellose, magnesium stearate, microcrystalline cellulose, polydextrose, titanium dioxide, triethyl citrate and FD&C Yellow #6.

Each Ranitidine Tablets, USP 300 mg for oral administration contains 334.8 mg of ranitidine HCl equivalent to 300 mg of ranitidine. Each tablet also contains the inactive ingredients colloidal silicon dioxide, croscarmellose sodium, hypromellose, magnesium stearate, microcrystalline cellulose, polydextrose, titanium dioxide, triethyl citrate and D&C Yellow #10.

CLINICAL PHARMACOLOGY

Ranitidine Tablets, USP are a competitive, reversible inhibitor of the action of histamine at the histamine H2-receptors, including receptors on the gastric cells. Ranitidine Tablets, USP do not lower serum Ca++ in hypercalcemic states. Ranitidine Tablets, USP are not an anticholinergic agent.

Pharmacokinetics: Absorption: Ranitidine Tablets, USP are 50% absorbed after oral administration, compared to an intravenous (IV) injection with mean peak levels of 440 to 545 ng/mL occurring 2 to 3 hours after a 150-mg dose. Absorption is not significantly impaired by the administration of food or antacids. Propantheline slightly delays and increases peak blood levels of ranitidine, probably by delaying gastric emptying and transit time. In one study, simultaneous administration of high-potency antacid (150 mmol) in fasting subjects has been reported to decrease the absorption of Ranitidine Tablets, USP.

Distribution: The volume of distribution is about 1.4 L/kg. Serum protein binding averages 15%.

Metabolism: In humans, the N-oxide is the principal metabolite in the urine; however, this amounts to <4% of the dose. Other metabolites are the S-oxide (1%) and the desmethyl ranitidine (1%). The remainder of the administered dose is found in the stool. Studies in patients with hepatic dysfunction (compensated cirrhosis) indicate that there are minor, but clinically insignificant, alterations in ranitidine half-life, distribution, clearance, and bioavailability.

Excretion: The principal route of excretion is the urine, with approximately 30% of the orally administered dose collected in the urine as unchanged drug in 24 hours. Renal clearance is about 410 mL/min, indicating active tubular excretion. The elimination half-life is 2.5 to 3 hours. Four patients with clinically significant renal function impairment (creatinine clearance 25 to 35 mL/min) administered 50 mg of ranitidine intravenously had an average plasma half-life of 4.8 hours, a ranitidine clearance of 29 mL/min, and a volume of distribution of 1.76 L/kg. In general, these parameters appear to be altered in proportion to creatinine clearance (see DOSAGE AND ADMINISTRATION).

Geriatrics: The plasma half-life is prolonged and total clearance is reduced in the elderly population due to a decrease in renal function. The elimination half-life is 3 to 4 hours. Peak levels average 526 ng/mL following a 150-mg twice daily dose and occur in about 3 hours (see PRECAUTIONS: Geriatric Use and DOSAGE AND ADMINISTRATION : Dosage Adjustment for Patients With Impaired Renal Function).

Pediatrics: There are no significant differences in the pharmacokinetic parameter values for ranitidine in pediatric patients (from 1 month up to 16 years of age) and healthy adults when correction is made for body weight. The average bioavailability of ranitidine given orally to pediatric patients is 48% which is comparable to the bioavailability of ranitidine in the adult population. All other pharmacokinetic parameter values (t1/2 , Vd, and CL) are similar to those observed with intravenous ranitidine use in pediatric patients. Estimates of Cmax and Tmax are displayed in Table 1.

Table 1. Ranitidine Pharmacokinetics in Pediatric Patients Following Oral Dosing
Population (age) | n | Dosage Form (dose) | Cmax (ng/mL | Tmax (hours)
Gastric or duodenal ulcer (3.5 to 16 years) | 12 | Tablets (1 to 2 mg/kg) | 54 to 492 | 2
Otherwise healthy requiring Ranitidine (0.7 to 14 years, Single dose) | 10 | Syrup (2 mg/kg) | 244 | 1.61
Otherwise healthy requiring Ranitidine (0.7 to 14 years, Multiple dose) | 10 | Syrup (2 mg/kg) | 320 | 1.66

Plasma clearance measured in 2 neonatal patients (less than 1 month of age) was considerably lower (3 mL/min/kg) than children or adults and is likely due to reduced renal function observed in this population (see PRECAUTIONS : Pediatric Use and DOSAGE AND ADMINISTRATION: Pediatric Use).

Pharmacodynamics: Serum concentrations necessary to inhibit 50% of stimulated gastric acid secretion are estimated to be 36 to 94 ng/mL. Following a single oral dose of 150 mg, serum concentrations of ranitidine are in this range up to 12 hours. However, blood levels bear no consistent relationship to dose or degree of acid inhibition.

Antisecretory Activity: 1. Effects on Acid Secretion: Ranitidine Tablets, USP inhibit both daytime and nocturnal basal gastric acid secretions as well as gastric acid secretion stimulated by food, betazole, and pentagastrin, as shown in Table 2.

Table 2. Effect of Oral Ranitidine Tablets, USP on Gastric Acid Secretion
 | Time After Dose, hours | % Inhibition of Gastric Acid Output by Dose, mg
 | Time After Dose, hours | 75 to 80 | 100 | 150 | 200
Basal | Up to 4 |  | 99 | 95
Nocturnal | Up to 13 | 95 | 96 | 92
Betazole | Up to 3 |  | 97 | 99
Pentagastrin | Up to 5 | 58 | 72 | 72 | 80
Meal | Up to 3 |  | 73 | 79 | 95

It appears that basal-, nocturnal-, and betazole-stimulated secretions are most sensitive to inhibition by Ranitidine Tablets, USP, responding almost completely to doses of 100 mg or less, while pentagastrin- and food-stimulated secretions are more difficult to suppress.

2. Effects on Other Gastrointestinal Secretions:

Pepsin: Oral Ranitidine Tablets, USP do not affect pepsin secretion. Total pepsin output is reduced in proportion to the decrease in volume of gastric juice.

Intrinsic Factor: Oral Ranitidine Tablets, USP have no significant effect on pentagastrin-stimulated intrinsic factor secretion.

Serum Gastrin: Ranitidine Tablets, USP have little or no effect on fasting or postprandial serum gastrin.

Other Pharmacologic Actions:

1. Gastric bacterial flora-increase in nitrate-reducing organisms, significance not known.
2. Prolactin levels-no effect in recommended oral or intravenous (IV) dosage, but small, transient, dose-related increases in serum prolactin have been reported after IV bolus injections of 100 mg or more.
3. Other pituitary hormones-no effect on serum gonadotropins, TSH, or GH. Possible impairment of vasopressin release.
4. No change in cortisol, aldosterone, androgen, or estrogen levels.
5. No antiandrogenic action.
6. No effect on count, motility, or morphology of sperm.

Pediatrics: Oral doses of 6 to 10 mg/kg/day in two or three divided doses maintain gastric pH>4 throughout most of the dosing interval.

Clinical Trials: Active Duodenal Ulcer: In a multicenter, double-blind, controlled, US study of endoscopically diagnosed duodenal ulcers, earlier healing was seen in the patients treated with Ranitidine Tablets, USP as shown in Table 3.

Table 3. Duodenal Ulcer Patient Healing Rates
 | Ranitidine Tablets, USP * |  | Placebo*
 | Number Entered | Healed / Evaluable | Number Entered | Healed / Evaluable
Outpatients | 195 | 69/182 (38%) † | 188 | 31-164 (19%)
Week 2 | 195 | 69/182 (38%) † | 188 | 31-164 (19%)
Week 4 | 195 | 137/187 (73%) † | 188 | 76/168 (45%)

*All patients were permitted antacids as needed for relief of pain.

†P<0.0001.

In these studies, patients treated with Ranitidine Tablets, USP reported a reduction in both daytime and nocturnal pain, and they also consumed less antacid than the placebo-treated patients.

Table 4. Mean Daily Doses of Antacid
 | Ulcer Healed | Ulcer Not Healed
Ranitidine | 0.06 | 0.71
Placebo | 0.71 | 1.43

Foreign studies have shown that patients heal equally well with 150 mg twice daily and 300 mg at bedtime (85% versus 84%, respectively) during a usual 4-week course of therapy. If patients require extended therapy of 8 weeks, the healing rate may be higher for 150 mg twice daily as compared to 300 mg at bedtime (92% versus 87%, respectively).

Studies have been limited to short-term treatment of acute duodenal ulcer. Patients whose ulcers healed during therapy had recurrences of ulcers at the usual rates.

Maintenance Therapy in Duodenal Ulcer: Ranitidine has been found to be effective as maintenance therapy for patients following healing of acute duodenal ulcers. In 2 independent, double-blind, multicenter, controlled trials, the number of duodenal ulcers observed was significantly less in patients treated with Ranitidine Tablets, USP (150 mg at bedtime) than in patients treated with placebo over a 12-month period.

Table 5. Duodenal Ulcer Prevalence
Double-Blind, Multicenter, Placebo-Controlled Trials
Multicenter Trial | Drug | Duodenal Ulcer Prevalence |  |  | No. of Patients
 |  | 0 to 4 Months | 0 to 8 Months | 0 to 12 Months
USA | RAN | 20%* | 24%* | 35%* | 138
USA | PLC | 44% | 54% | 59% | 139
Foreign | RAN | 12%* | 21%* | 28%* | 174
Foreign | PLC | 56% | 64% | 68% | 165

% = Life table estimate.

* = P<0.05 (Ranitidine Tablets, USP versus comparator).

RAN = ranitidine (Ranitidine Tablets, USP)

PLC = placebo.

As with other H2-antagonists, the factors responsible for the significant reduction in the prevalence of duodenal ulcers include prevention of recurrence of ulcers, more rapid healing of ulcers that may occur during maintenance therapy, or both.

Gastric Ulcer: In a multicenter, double-blind, controlled, US study of endoscopically diagnosed gastric ulcers, earlier healing was seen in the patients treated with Ranitidine Tablets, USP as shown in Table 6.

Table 6. Gastric Ulcer Patient Healing Rates
 | Ranitidine Tablets, USP* |  | Placebo*
 | Number Entered | Healed / Evaluable | Number Entered | Healed / Evaluable
Outpatients | 92 | 16/83 (19%) † | 94 | 10/83 (12%)
Week 2 | 92 | 16/83 (19%) † | 94 | 10/83 (12%)
Week 6 | 92 | 50/73 (68%) † | 94 | 35/69 (51%)

*All patients were permitted antacids as needed for relief of pain.

†P = 0.009.

In this multicenter trial, significantly more patients treated with Ranitidine Tablets, USP became pain free during therapy.

Maintenance of Healing of Gastric Ulcers: In two multicenter, double-blind, randomized, placebo-controlled, 12-month trials conducted in patients whose gastric ulcers had been previously healed, Ranitidine Tablets, USP 150 mg at bedtime was significantly more effective than placebo in maintaining healing of gastric ulcers.

Pathological Hypersecretory Conditions (such as Zollinger-Ellison syndrome):

Ranitidine Tablets, USP inhibits gastric acid secretion and reduces occurrence of diarrhea, anorexia, and pain in patients with pathological hypersecretion associated with Zollinger-Ellison syndrome, systemic mastocytosis, and other pathological hypersecretory conditions (e.g., postoperative, "short-gut" syndrome, idiopathic). Use of Ranitidine Tablets, USP was followed by healing of ulcers in 8 of 19 (42%) patients who were intractable to previous therapy.

Gastroesophageal Reflux Disease (GERD): In 2 multicenter, double-blind, placebo-controlled, 6-week trials performed in the United States and Europe, Ranitidine Tablets, USP 150 mg twice daily was more effective than placebo for the relief of heartburn and other symptoms associated with GERD. Ranitidine-treated patients consumed significantly less antacid than did placebo-treated patients.

The US trial indicated that Ranitidine Tablets, USP 150 mg twice daily significantly reduced the frequency of heartburn attacks and severity of heartburn pain within 1 to 2 weeks after starting therapy. The improvement was maintained throughout the 6-week trial period. Moreover, patient response rates demonstrated that the effect on heartburn extends through both the day and night time periods.

In two additional US multicenter, double-blind, placebo-controlled, 2-week trials, Ranitidine Tablets, USP 150 mg twice daily was shown to provide relief of heartburn pain within 24 hours of initiating therapy and a reduction in the frequency of severity of heartburn.

Erosive Esophagitis: In two multicenter, double-blind, randomized, placebo-controlled, 12-week trials performed in the United States, Ranitidine Tablets, USP 150 mg four times daily was significantly more effective than placebo in healing endoscopically diagnosed erosive esophagitis and in relieving associated heartburn.

The erosive esophagitis healing rates were as follows:

Table 7. Erosive Esophagitis Patient Healing Rates
 | Healed / Evaluable
 | Placebo* n=229 | Ranitidine Tablets, USP 150 mg 4 times daily* n=215
Week 4 | 43/198 (22%) | 96/206 (47%) †
Week 8 | 63/176 (36%) | 142/200 (71%) †
Week 12 | 92/159 (58%) | 162/192 (84%) †

*All patients were permitted antacids as needed for relief of pain.

†P<0.001 versus placebo.

No additional benefit in healing of esophagitis or in relief of heartburn was seen with a ranitidine dose of 300 mg 4 times daily.

Maintenance of Healing of Erosive Esophagitis: In 2 multicenter, double-blind, randomized, placebo-controlled, 48-week trials conducted in patients whose erosive esophagitis had been previously healed, Ranitidine Tablets, USP 150 mg twice daily was significantly more effective than placebo in maintaining healing of erosive esophagitis.

INDICATIONS AND USAGE

Ranitidine Tablets, USP are indicated in:

1. Short-term treatment of active duodenal ulcer. Most patients heal within 4 weeks. Studies available to date have not assessed the safety of ranitidine in uncomplicated duodenal ulcer for periods of more than 8 weeks.
2. Maintenance therapy for duodenal ulcer patients at reduced dosage after healing of acute ulcers. No placebo-controlled comparative studies have been carried out for periods of longer than 1 year.
3. The treatment of pathological hypersecretory conditions (e.g., Zollinger-Ellison syndrome and systemic mastocytosis).
4. Short-term treatment of active, benign gastric ulcer. Most patients heal within 6 weeks and the usefulness of further treatment has not been demonstrated. Studies available to date have not assessed the safety of ranitidine in uncomplicated, benign gastric ulcer for periods of more than 6 weeks.
5. Maintenance therapy for gastric ulcer patients at reduced dosage after healing of acute ulcers. Placebo-controlled studies have been carried out for 1 year.
6. Treatment of GERD. Symptomatic relief commonly occurs within 24 hours after starting therapy with Ranitidine Tablets, USP 150 mg b.i.d.
7. Treatment of endoscopically diagnosed erosive esophagitis. Symptomatic relief of heartburn commonly occurs within 24 hours of therapy initiation with Ranitidine Tablets, USP 150 mg q.i.d.
8. Maintenance of healing of erosive esophagitis. Placebo-controlled trials have been carried out for 48 weeks.

Concomitant antacids should be given as needed for pain relief to patients with active duodenal ulcer; active, benign gastric ulcer; hypersecretory states; GERD; and erosive esophagitis.

CONTRAINDICATIONS

Ranitidine Tablets, USP are contraindicated for patients known to have hypersensitivity to the drug or any of the ingredients (see PRECAUTIONS).

PRECAUTIONS

General:

1. Symptomatic response to therapy with Ranitidine Tablets, USP does not preclude the presence of gastric malignancy.
2. Since ranitidine is excreted primarily by the kidney, dosage should be adjusted in patients with impaired renal function (see DOSAGE AND ADMINISTRATION). Caution should be observed in patients with hepatic dysfunction since ranitidine is metabolized in the liver.
3. Rare reports suggest that ranitidine may precipitate acute porphyric attacks in patients with acute porphyria. Ranitidine should therefore be avoided in patients with a history of acute porphyria.

Laboratory Tests: False-positive tests for urine protein with MULTISTIX® may occur during therapy with Ranitidine Tablets, USP, and therefore testing with sulfosalicylic acid is recommended.

Drug Interactions: Ranitidine Tablets, USP have been reported to affect the bioavailability of other drugs through several different mechanisms such as competition for renal tubular secretion, alteration of gastric pH, and inhibition of cytochrome P450 enzymes.

Procainamide: Ranitidine, a substrate of the renal organic cation transport system, may affect the clearance of other drugs eliminated by this route. High doses of ranitidine (e.g., such as those used in the treatment of Zollinger-Ellison syndrome) have been shown to reduce the renal excretion of procainamide and N-acetylprocainamide resulting in increased plasma levels of these drugs. Although this interaction is unlikely to be clinically relevant at usual ranitidine doses, it may be prudent to monitor for procainamide toxicity when administered with oral ranitidine at a dose exceeding 300 mg per day.

Warfarin: There have been reports of altered prothrombin time among patients on concomitant warfarin and ranitidine therapy. Due to the narrow therapeutic index, close monitoring of increased or decreased prothrombin time is recommended during concurrent treatment with ranitidine.

Ranitidine may alter the absorption of drugs in which gastric pH is an important determinant of bioavailability. This can result in either an increase in absorption (e.g., triazolam, midazolam, glipizide) or a decrease in absorption (e.g., ketoconazole, atazanavir, delavirdine, gefitinib). Appropriate clinical monitoring is recommended.

Atazanavir: Atazanavir absorption may be impaired based on known interactions with other agents that increase gastric pH. Use with caution. See atazanavir label for specific recommendations.

Delavirdine: Delavirdine absorption may be impaired based on known interactions with other agents that increase gastric pH. Chronic use of H2-receptor antagonists with delavirdine is not recommended.

Gefitinib: Gefitinib exposure was reduced by 44% with the co-administration of ranitidine and sodium bicarbonate (dosed to maintain gastric pH above 5.0). Use with caution.

Glipizide: In diabetic patients, glipizide exposure was increased by 34% following a single 150-mg dose of oral ranitidine. Use appropriate clinical monitoring when initiating or discontinuing ranitidine.

Ketoconazole: Oral ketoconazole exposure was reduced by up to 95% when oral ranitidine was co-administered in a regimen to maintain a gastric pH of 6 or above. The degree of interaction with usual dose of ranitidine (150 mg twice daily) is unknown.

Midazolam: Oral midazolam exposure in 5 healthy volunteers was increased by up to 65% when administered with oral ranitidine at a dose of 150 mg twice daily. However, in another interaction study in 8 volunteers receiving IV midazolam, a 300 mg oral dose of ranitidine increased midazolam exposure by about 9%. Monitor patients for excessive or prolonged sedation when ranitidine is co-administered with oral midazolam.

Triazolam: Triazolam exposure in healthy volunteers was increased by approximately 30% when administered with oral ranitidine at a dose of 150 mg twice daily. Monitor patients for excessive or prolonged sedation.

Carcinogenesis, Mutagenesis, Impairment of Fertility: There was no indication of tumorigenic or carcinogenic effects in life-span studies in mice and rats at dosages up to 2,000 mg/kg/day.

Ranitidine was not mutagenic in standard bacterial tests (Salmonella, Escherichia coli) for mutagenicity at concentrations up to the maximum recommended for these assays. In a dominant lethal assay, a single oral dose of 1,000 mg/kg to male rats was without effect on the outcome of 2 matings per week for the next 9 weeks.

Pregnancy: Teratogenic Effects: Pregnancy Category B. Reproduction studies have been performed in rats and rabbits at doses up to 160 times the human dose and have revealed no evidence of impaired fertility or harm to the fetus due to Ranitidine Tablets, USP. There are, however, no adequate and well-controlled studies in pregnant women. Because animal reproduction studies are not always predictive of human response, this drug should be used during pregnancy only if clearly needed.

Nursing Mothers: Ranitidine is secreted in human milk. Caution should be exercised when Ranitidine Tablets, USP is administered to a nursing mother.

Pediatric Use: The safety and effectiveness of Ranitidine Tablets, USP have been established in the age-group of 1 month to 16 years for the treatment of duodenal and gastric ulcers, gastroesophageal reflux disease and erosive esophagitis, and the maintenance of healed duodenal and gastric ulcer. Use of Ranitidine Tablets, USP in this age-group is supported by adequate and well-controlled studies in adults, as well as additional pharmacokinetic data in pediatric patients and an analysis of the published literature (see CLINICAL PHARMACOLOGY: Pediatrics and DOSAGE AND ADMINISTRATION: Pediatric Use).

Safety and effectiveness in pediatric patients for the treatment of pathological hypersecretory conditions or the maintenance of healing of erosive esophagitis have not been established.

Safety and effectiveness in neonates (less than 1 month of age) have not been established (see CLINICAL PHARMACOLOGY: Pediatrics)

Geriatric Use: Of the total number of subjects enrolled in US and foreign controlled clinical trials of oral formulations of Ranitidine Tablets, USP, for which there were subgroup analyses, 4,197 were 65 and over, while 899 were 75 and over. No overall differences in safety or effectiveness were observed between these subjects and younger subjects, and other reported clinical experience has not identified differences in responses between the elderly and younger patients, but greater sensitivity of some older individuals cannot be ruled out.

This drug is known to be substantially excreted by the kidney and the risk of toxic reactions to this drug may be greater in patients with impaired renal function. Because elderly patients are more likely to have decreased renal function, caution should be exercised in dose selection, and it may be useful to monitor renal function (see CLINICAL PHARMACOLOGY: Pharmacokinetics: Geriatrics and DOSAGE AND ADMINISTRATION: Dosage Adjustment for Patients With Impaired Renal Function).

ADVERSE REACTIONS

The following have been reported as events in clinical trials or in the routine management of patients treated with Ranitidine Tablets, USP. The relationship to therapy with Ranitidine Tablets, USP has been unclear in many cases. Headache, sometimes severe, seems to be related to administration of Ranitidine Tablets, USP.

Central Nervous System: Rarely, malaise, dizziness, somnolence, insomnia, and vertigo. Rare cases of reversible mental confusion, agitation, depression, and hallucinations have been reported, predominantly in severely ill elderly patients. Rare cases of reversible blurred vision suggestive of a change in accommodation have been reported. Rare reports of reversible involuntary motor disturbances have been received.

Cardiovascular: As with other H2-blockers, rare reports of arrhythmias such as tachycardia, bradycardia, atrioventricular block, and premature ventricular beats.

Gastrointestinal: Constipation, diarrhea, nausea/vomiting, abdominal discomfort/pain, and rare reports of pancreatitis.

Hepatic: There have been occasional reports of hepatocellular, cholestatic, or mixed hepatitis, with or without jaundice. In such circumstances, ranitidine should be immediately discontinued. These events are usually reversible, but in rare circumstances death has occurred. Rare cases of hepatic failure have also been reported. In normal volunteers, SGPT values were increased to at least twice the pretreatment levels in 6 of 12 subjects receiving 100 mg intravenously 4 times daily for 7 days, and in 4 of 24 subjects receiving 50 mg intravenously 4 times daily for 5 days.

Musculoskeletal: Rare reports of arthralgias and myalgias.

Hematologic: Blood count changes (leukopenia, granulocytopenia, and thrombocytopenia) have occurred in a few patients. These were usually reversible. Rare cases of agranulocytosis, pancytopenia, sometimes with marrow hypoplasia, and aplastic anemia and exceedingly rare cases of acquired immune hemolytic anemia have been reported.

Endocrine: Controlled studies in animals and man have shown no stimulation of any pituitary hormone by Ranitidine Tablets, USP and no antiandrogenic activity, and cimetidine-induced gynecomastia and impotence in hypersecretory patients have resolved when Ranitidine Tablets, USP have been substituted. However, occasional cases of impotence and loss of libido have been reported in male patients receiving Ranitidine Tablets, USP, but the incidence did not differ from that in the general population.

Rare cases of breast symptoms and conditions, including galactorrhea and gynecomastia, have been reported in both males and females.

Integumentary: Rash, including rare cases of erythema multiforme. Rare cases of alopecia and vasculitis.

Respiratory: A large epidemiological study suggested an increased risk of developing pneumonia in current users of histamine-2-receptor antagonists (H2RAs) compared to patients who had stopped H2RA treatment, with an observed adjusted relative risk of 1.63 (95% CI, 1.07 to 2.48). However, a causal relationship between use of H2RAs and pneumonia has not been established.

Other: Rare cases of hypersensitivity reactions (e.g., bronchospasm, fever, rash, eosinophilia), anaphylaxis, angioneurotic edema, acute interstitial nephritis, and small increases in serum creatinine.

OVERDOSAGE

There has been limited experience with overdosage. Reported acute ingestions of up to 18 g orally have been associated with transient adverse effects similar to those encountered in normal clinical experience (see ADVERSE REACTIONS). In addition, abnormalities of gait and hypotension have been reported.

When overdosage occurs, the usual measures to remove unabsorbed material from the gastrointestinal tract, clinical monitoring, and supportive therapy should be employed.

Studies in dogs receiving dosages of Ranitidine Tablets, USP in excess of 225 mg/kg/day have shown muscular tremors, vomiting, and rapid respiration. Single oral doses of 1,000 mg/kg in mice and rats were not lethal. Intravenous LD50 values in mice and rats were 77 and 83 mg/kg, respectively.

DOSAGE AND ADMINISTRATION

Active Duodenal Ulcer: The current recommended adult oral dosage of Ranitidine Tablets, USP for duodenal ulcer is 150 mg twice daily. An alternative dosage of 300 mg once daily after the evening meal or at bedtime can be used for patients in whom dosing convenience is important. The advantages of one treatment regimen compared to the other in a particular patient population have yet to be demonstrated (see Clinical Trials: Active Duodenal Ulcer). Smaller doses have been shown to be equally effective in inhibiting gastric acid secretion in US studies, and several foreign trials have shown that 100 mg twice daily is as effective as the 150-mg dose. Antacid should be given as needed for relief of pain (see CLINICAL PHARMACOLOGY: Pharmacokinetics).

Maintenance of Healing of Duodenal Ulcers: The current recommended adult oral dosage is 150 mg at bedtime.

Pathological Hypersecretory Conditions (such as Zollinger-Ellison syndrome):

The current recommended adult oral dosage is 150 mg twice daily. In some patients it may be necessary to administer Ranitidine Tablets, USP 150-mg doses more frequently. Dosages should be adjusted to individual patient needs, and should continue as long as clinically indicated. Dosages up to 6 g/day have been employed in patients with severe disease.

Benign Gastric Ulcer: The current recommended adult oral dosage is 150 mg twice daily.

Maintenance of Healing of Gastric Ulcers: The current recommended adult oral dosage is 150 mg at bedtime.

GERD: The current recommended adult oral dosage is 150 mg twice daily.

Erosive Esophagitis: The current recommended adult oral dosage is 150 mg four times daily.

Maintenance of Healing of Erosive Esophagitis: The current recommended adult oral dosage is 150 mg twice daily.

Pediatric Use: The safety and effectiveness of Ranitidine Tablets, USP have been established in the age-group of 1 month to 16 years. There is insufficient information about the pharmacokinetics of Ranitidine Tablets, USP in neonatal patients (less than 1 month of age) to make dosing recommendations.

The following 3 subsections provide dosing information for each of the pediatric indications.

Treatment of Duodenal and Gastric Ulcers: The recommended oral dose for the treatment of active duodenal and gastric ulcers is 2 to 4 mg/kg twice daily to a maximum of 300 mg/day. This recommendation is derived from adult clinical studies and pharmacokinetic data in pediatric patients.

Maintenance of Healing of Duodenal and Gastric Ulcers: The recommended oral dose for the maintenance of healing of duodenal and gastric ulcers is 2 to 4 mg/kg once daily to a maximum of 150 mg/day. This recommendation is derived from adult clinical studies and pharmacokinetic data in pediatric patients.

Treatment of GERD and Erosive Esophagitis: Although limited data exist for these conditions in pediatric patients, published literature supports a dosage of 5 to 10 mg/kg/day, usually given as two divided doses.

Dosage Adjustment for Patients With Impaired Renal Function: On the basis of experience with a group of subjects with severely impaired renal function treated with Ranitidine Tablets, USP, the recommended dosage in patients with a creatinine clearance <50 mL/min is 150 mg every 24 hours. Should the patient's condition require, the frequency of dosing may be increased to every 12 hours or even further with caution. Hemodialysis reduces the level of circulating ranitidine. Ideally, the dosing schedule should be adjusted so that the timing of a scheduled dose coincides with the end of hemodialysis.

Elderly patients are more likely to have decreased renal function, therefore caution should be exercised in dose selection, and it may be useful to monitor renal function (see CLINICAL PHARMACOLOGY: Pharmacokinetics: Geriatrics and PRECAUTIONS: Geriatric Use).

HOW SUPPLIED

Ranitidine Tablets, USP 150 mg (ranitidine HCl equivalent to 150 mg of ranitidine) are supplied as orange, round, biconvex aqueous film-coated tablets debossed “IP 253” on one side and plain on the reverse.

They are available as follows:

Bottles of 60: NDC 53746-253-60

Bottles of 100: NDC 53746-253-01

Bottles of 180: NDC 53746-253-18

Bottles of 500: NDC 53746-253-05

Bottles of 1000: NDC 53746-253-10

Ranitidine Tablets, USP 300 mg (ranitidine HCl equivalent to 300 mg of ranitidine) are supplied as yellow, capsule-shaped aqueous film-coated tablets debossed “IP 254” on one side and plain on the reverse.

They are available as follows:

Bottles of 30: NDC 53746-254-30

Bottles of 100: NDC 53746-254-01

Bottles of 250: NDC 53746-254-02

Store at 20° to 25°C (68° to 77°F) [See USP Controlled Room Temperature] in a dry place. Dispense in a tight, light-resistant container as defined in the USP. Protect from light. Replace cap securely after each opening.

Distributed by:
Amneal Pharmaceuticals
Bridgewater, NJ 08807

Rev. 09-2015-02

PACKAGE LABEL.PRINCIPAL DISPLAY PANEL

Label 150 mg

PACKAGE LABEL PRINCIPAL DISPLAY PANEL

Label 300 mg